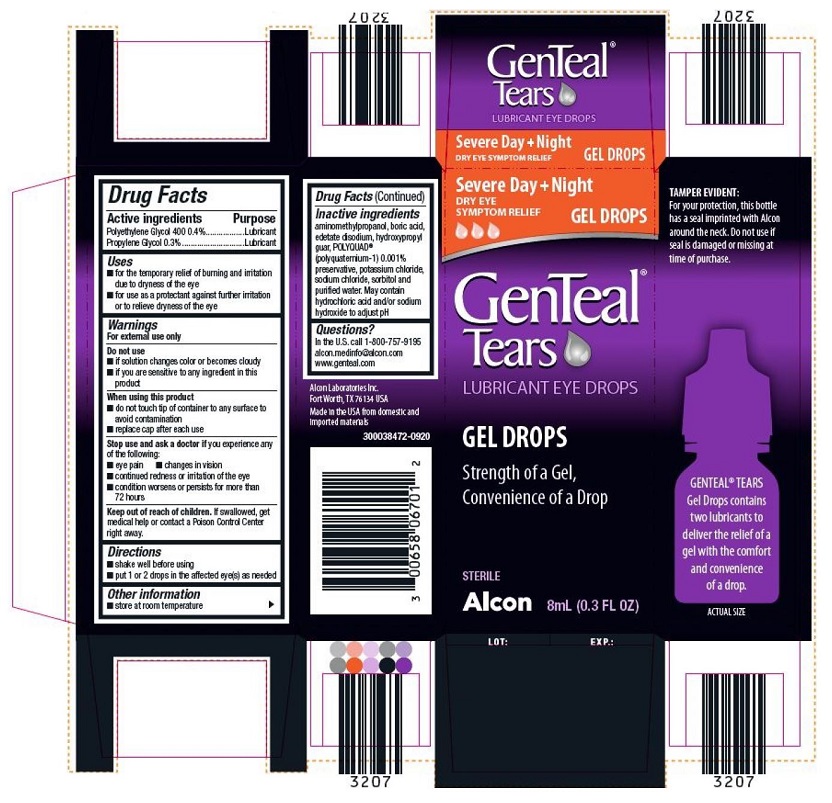 DRUG LABEL: GenTeal Tears Gel Drops
NDC: 0065-8067 | Form: GEL
Manufacturer: Alcon Laboratories, Inc.
Category: otc | Type: HUMAN OTC DRUG LABEL
Date: 20231214

ACTIVE INGREDIENTS: Polyethylene Glycol 400 4 mg/1 mL; Propylene Glycol 3 mg/1 mL
INACTIVE INGREDIENTS: Aminomethylpropanol; Boric Acid; Edetate Disodium; Guaraprolose (3500 Mpa.S At 1%); Polidronium Chloride; Potassium Chloride; Sodium Chloride; Sorbitol; Water; Hydrochloric Acid; Sodium Hydroxide

Drug Facts

ACTIVE INGREDIENT

Active Ingredients | Purpose
Polyethylene Glycol 400 0.4% | Lubricant
Propylene Glycol 0.3% | Lubricant

Uses

- for the temporary relief of burning and irritation due to dryness of the eye
- for use as a protectant against further irritation or to relieve dryness of the eye

Warnings

For external use only

Do not use

- if this product changes color or becomes cloudy
- if you are sensitive to any ingredient in this product

When using this product

- do not touch tip of container to any surface to avoid contamination
- replace cap after each use

Stop use and ask a doctor if you experience any of the following:

- eye pain
- changes in vision
- continued redness or irritation of the eye
- condition worsens or persists for more than 72 hours

Keep out of reach of children. If swallowed, get medical help or contact a Poison Control Center right away.

Directions

- shake well before using
- put 1 or 2 drops in the affected eye(s) as needed

Other information

- store at room temperature

Inactive ingredients

Aminomethylpropanol, boric acid, edetate disodium, hydroxypropyl guar, POLYQUAD® (polyquaternium-1) 0.001% preservative, potassium chloride, sodium chloride, sorbitol and purified water. May contain hydrochloric acid and /or sodium hydroxide to adjust pH.

Questions?

In the U.S. call
1-800-757-9195
alcon.medinfo@alcon.com
www.genteal.com
Alcon Laboratories Inc.
Fort Worth, TX 76134 USA
Made in the USA from domestic and imported materials

300038472-0920
TOP OF THE CARTON
GenTeal® Tears
LUBRICANT EYE DROPS
Severe Day + Night
DRY EYE SYMPTOM RELIEF GEL DROPS

PRINCIPAL DISPLAY PANEL

Severe Day + Night
DRY EYE SYMPTOM RELIEF GEL DROPS
GenTeaL® Tears
LUBRICANT EYE DROPS
GEL DROPS
Strength of a Gel,
Convenience of a drop
STERILE
Alcon 8ml (0.3 FL OZ)
TAMPER EVIDENT:
For your protection, this bottle has a seal imprinted with Alcon around the neck. Do not use if seal is damaged or missing at time of purchase.
GENTEAL® TEARS Gel Drops contains two lubricants to deliver the relief of a gel with the comfort and convenience of a drop.